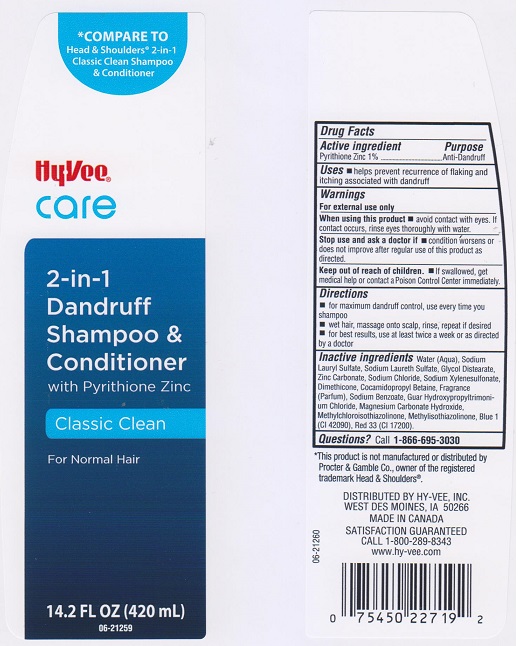 DRUG LABEL: Hyvee Care Classic Clean 2 in 1 Dandruff
NDC: 42507-424 | Form: SHAMPOO
Manufacturer: Hyvee Inc
Category: otc | Type: HUMAN OTC DRUG LABEL
Date: 20160614

ACTIVE INGREDIENTS: PYRITHIONE ZINC 10 mg/1 mL
INACTIVE INGREDIENTS: WATER; SODIUM LAURYL SULFATE; SODIUM LAURETH SULFATE; GLYCOL DISTEARATE; ZINC CARBONATE; SODIUM CHLORIDE; SODIUM XYLENESULFONATE; DIMETHICONE; COCAMIDOPROPYL BETAINE; SODIUM BENZOATE; MAGNESIUM CARBONATE HYDROXIDE; METHYLCHLOROISOTHIAZOLINONE; METHYLISOTHIAZOLINONE; FD&C BLUE NO. 1; D&C RED NO. 33

DRUG FACTS

Active ingredient

Pyrithione Zinc 1%

Purpose

Anti-dandruff

Uses

- helps prevent recurrence of flaking and itching associated with dandruff.

Warnings

For external use only.

When using this product

- avoid contact with eyes. If contact occurs, rinse eyes thoroughly with water.

Stop use and ask a doctor if

- condition worsens or does not improve after regular use of this product as directed.

Keep out of reach of children.

- If swallowed, get medical help or contact a Poison Control Center immediately.

Directions

- for maximum dandruff control, use every time you shampoo.
- wet hair, massage onto scalp, rinse, repeat if desired.
- for best results, use at least twice a week or as directed by a doctor.

Inactive ingredients

Water (Aqua), Sodium Lauryl Sulfate, Sodium Laureth Sulfate, Glycol Distearate, Zinc Carbonate, Sodium Chloride, Sodium Xylenesulfonate, Dimethicone, Cocamidopropyl Betaine, Fragrance (Parfum), Sodium Benzoate, Guar Hydroxypropyltrimonium Chloride, Magnesium Carbonate Hydroxide, Methylchloroisothiazolinone, Methylisothiazolinone, Blue 1 (CI 42090), Red 33 (CI 17200).

Questions?

Call 1-866-695-3030